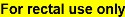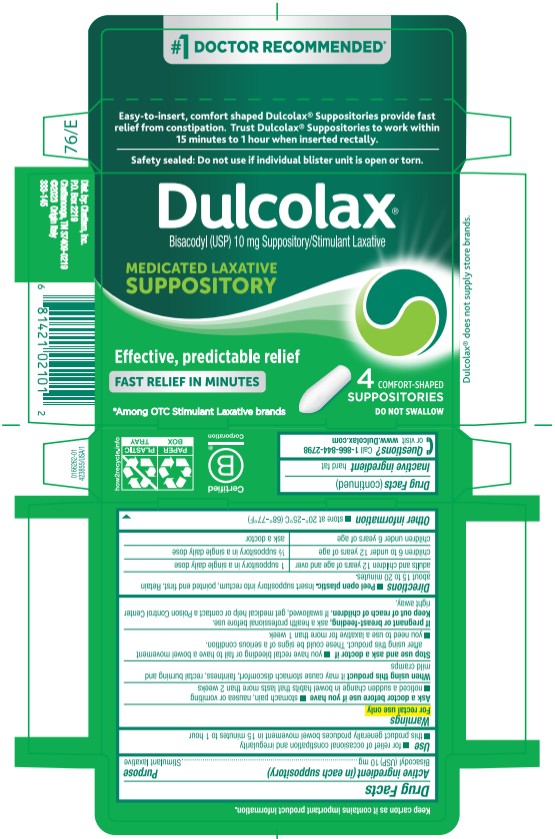 DRUG LABEL: Dulcolax Laxative
NDC: 41167-0210 | Form: SUPPOSITORY
Manufacturer: Chattem, Inc.
Category: otc | Type: HUMAN OTC DRUG LABEL
Date: 20240201

ACTIVE INGREDIENTS: BISACODYL 10 mg/1 1
INACTIVE INGREDIENTS: FAT, HARD

Dulcolax Medicated Laxative Suppository

Dulcolax®

Medicated Laxative Suppositories

Drug Facts

Active ingredient (in each suppository)

Bisacodyl (USP) 10 mg

Purpose

Stimulant laxative

Use

- for relief of occasional constipation and irregularity
- this product generally produces bowel movement in 15 minutes to 1 hour

Warnings

Ask a doctor before use if you have

- stomach pain, nausea or vomiting
- noticed a sudden change in bowel habits that lasts more than 2 weeks

When using this product

it may cause stomach discomfort, faintness, rectal burning and mild cramps

Stop use and ask a doctor if

- you have rectal bleeding or fail to have a bowel movement after using this product. These could be signs of a serious condition.
- you need to use a laxative for more than 1 week

If pregnant or breast-feeding,

ask a health professional before use.

Keep out of reach of children.

If swallowed, get medical help or contact a Poison Control Center right away.

Directions

- Peel open plastic. Insert suppository into rectum, pointed end first. Retain about 15 to 20 minutes.

adults and children 12 years of age and over | 1 suppository in a single daily dose.
children 6 to under 12 years of age | ½ suppository in a single daily dose
children under 6 years of age | ask a doctor

Other information

- store at 20°-25°C (68°-77°F)

Inactive ingredient

hard fat

Questions?

Call 1-866-844-2798 or visit www.Dulcolax.com

Keep carton as it contains important product information.

PRINCIPAL DISPLAY PANEL

Dulcolax
Bisacodyl (USP) 10 mg Suppository/ Stimulant Laxative
MEDICATED LAXATIVE
SUPPOSITORY
4 COMFORT SHAPED
SUPPOSITORIES
DO NOT SWALLOW